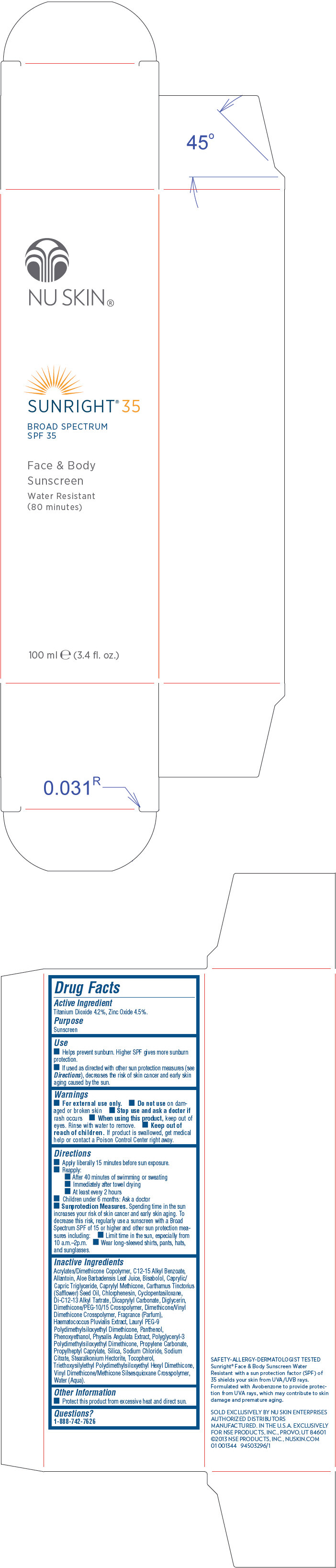 DRUG LABEL: Nu Skin Sunright 35 Broad Spectrum SPF 35
NDC: 62839-1344 | Form: LOTION
Manufacturer: NSE Products, Inc.
Category: otc | Type: HUMAN OTC DRUG LABEL
Date: 20220114

ACTIVE INGREDIENTS: Titanium Dioxide 42 mg/1 mL; Zinc Oxide 45 mg/1 mL
INACTIVE INGREDIENTS: Alkyl (C12-15) Benzoate; Allantoin; Aloe Vera Leaf; Levomenol; Medium-Chain Triglycerides; Caprylyl Trisiloxane; Safflower Oil; Chlorphenesin; Cyclomethicone 5; Di-C12-13 Alkyl Tartrate; Dicaprylyl Carbonate; Diglycerin; Dimethicone; Haematococcus Pluvialis; Lauryl PEG-9 Polydimethylsiloxyethyl Dimethicone; Panthenol; Phenoxyethanol; Physalis Angulata whole; Propylene Carbonate; Propylheptyl Caprylate; Silicon Dioxide; Sodium Chloride; Sodium Citrate, Unspecified Form; Stearalkonium Hectorite; Tocopherol; Water

Nu Skin® Sunright® 35 Broad Spectrum SPF 35

Drug Facts

Active Ingredient

Titanium Dioxide 4.2%, Zinc Oxide 4.5%.

Purpose

Sunscreen

Use

- Helps prevent sunburn. Higher SPF gives more sunburn protection.
- If used as directed with other sun protection measures (see Directions), decreases the risk of skin cancer and early skin aging caused by the sun.

Warnings

- For external use only.

- Do not use on damaged or broken skin

- Stop use and ask a doctor if rash occurs

- When using this product, keep out of eyes. Rinse with water to remove.

- Keep out of reach of children. If product is swallowed, get medical help or contact a Poison Control Center right away.

Directions

- Apply liberally 15 minutes before sun exposure.
- Reapply:
  - After 40 minutes of swimming or sweating
  - Immediately after towel drying
  - At least every 2 hours
- Children under 6 months: Ask a doctor
- Sunprotection Measures. Spending time in the sun increases your risk of skin cancer and early skin aging. To decrease this risk, regularly use a sunscreen with a Broad Spectrum SPF of 15 or higher and other sun protection measures including:
  - Limit time in the sun, especially from 10 a.m.–2p.m.
  - Wear long-sleeved shirts, pants, hats, and sunglasses.

Inactive Ingredients

Acrylates/Dimethicone Copolymer, C12-15 Alkyl Benzoate, Allantoin, Aloe Barbadensis Leaf Juice, Bisabolol, Caprylic/Capric Triglyceride, Caprylyl Methicone, Carthamus Tinctorius (Safflower) Seed Oil, Chlorphenesin, Cyclopentasiloxane, Di-C12-13 Alkyl Tartrate, Dicaprylyl Carbonate, Diglycerin, Dimethicone/PEG-10/15 Crosspolymer, Dimethicone/Vinyl Dimethicone Crosspolymer, Fragrance (Parfum), Haematococcus Pluvialis Extract, Lauryl PEG-9 Polydimethylsiloxyethyl Dimethicone, Panthenol, Phenoxyethanol, Physalis Angulata Extract, Polyglyceryl-3 Polydimethylsiloxyethyl Dimethicone, Propylene Carbonate, Propylheptyl Caprylate, Silica, Sodium Chloride, Sodium Citrate, Stearalkonium Hectorite, Tocopherol, Triethoxysilylethyl Polydimethylsiloxyethyl Hexyl Dimethicone, Vinyl Dimethicone/Methicone Silsesquioxane Crosspolymer, Water (Aqua).

Other Information

- Protect this product from excessive heat and direct sun.

Questions?

1-888-742-7626

PRINCIPAL DISPLAY PANEL - 100 mL Bottle Carton

NU SKIN®

SUNRIGHT® 35

BROAD SPECTRUM
SPF 35

Face & Body
Sunscreen

Water Resistant
(80 minutes)

100 ml e (3.4 fl. oz.)